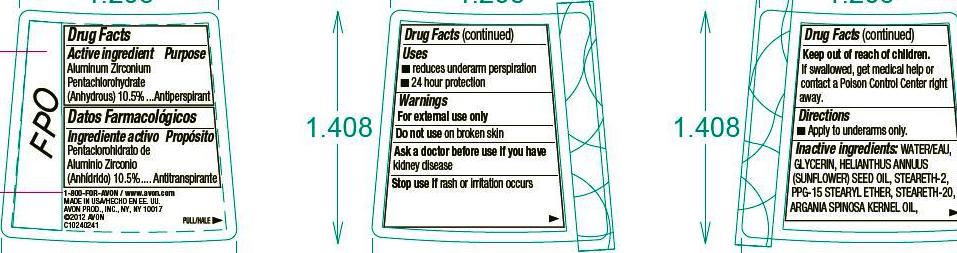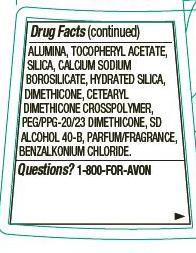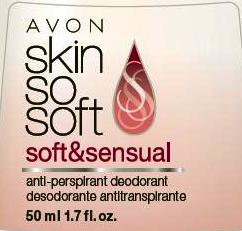 DRUG LABEL: Skin So Soft 
NDC: 10096-0271 | Form: GEL
Manufacturer: Avon Products, Inc.
Category: otc | Type: HUMAN OTC DRUG LABEL
Date: 20151218

ACTIVE INGREDIENTS: ALUMINUM ZIRCONIUM PENTACHLOROHYDRATE 105 mg/1 mL

Active ingredient
Aluminum Zirconium Pentachlorohydrate (Anhydrous) 10.5%...........

Purpose
.............Antiperspirant

Uses
• reduces underarm perspiration
• 24 hour protection

Warnings
For external use only

Do not use on broken skin

Ask a doctor before use if you have kidney disease

Stop use if rash or irritation occurs

Keep out of reach of children. If swallowed, get medical help or contact a Poison Control Center right away.

Directions
• apply to underarms only

INACTIVE INGREDIENT

Inactive ingredients: WATER/EAU, GLYCERIN, HELIANTHUS ANNUUS (SUNFLOWER) SEED OIL, STEARETH-2, PPG-15 STEARYL ETHER, STEARETH-20, ARGANIA SPINOSA KERNEL OIL,ALUMINA, TOCOPHERYL ACETATE, SILICA, CALCIUM SODIUM BOROSILICATE, HYDRATED SILICA, DIMETHICONE, CETEARYL DIMETHICONE CROSSPOLYMER, PEG/PPG-20/23 DIMETHICONE, SD ALCOHOL 40-B, PARFUM/FRAGRANCE, BENZALKONIUM CHLORIDE.

Questions?1-800-FOR-AVON